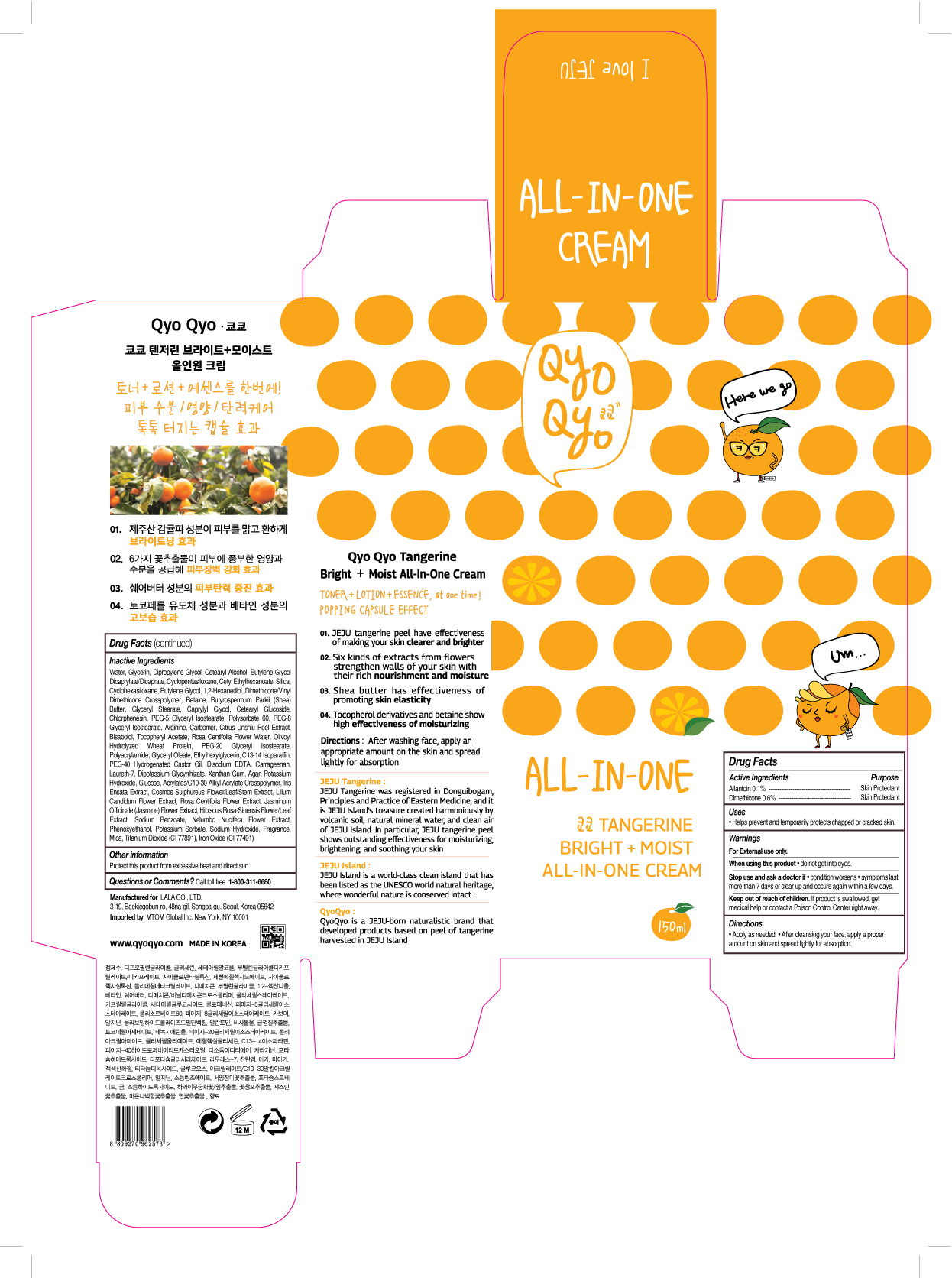 DRUG LABEL: QYO QYO Tangerine Bright Moist All In One Cream
NDC: 71733-101 | Form: LOTION
Manufacturer: LaLa Co., Ltd.
Category: otc | Type: HUMAN OTC DRUG LABEL
Date: 20190101

ACTIVE INGREDIENTS: DIMETHICONE 0.6 g/150 mL; ALLANTOIN 0.1 g/150 mL
INACTIVE INGREDIENTS: DIPROPYLENE GLYCOL; BUTYLENE GLYCOL; TANGERINE PEEL; WATER; GLYCERIN

Qyo Qyo Tangerine Bright + Moist
All In One Cream

ACTIVE INGREDIENTS

ALLANTOIN 0.1%

DIMETHICONE 0.6%

PURPOSE

SKIN PROTECTANT

USES

- Helps prevent and temporarily protects chapped or cracked skin.

WARNINGS

For external use only.

When using this product • do not get into eyes.

STOP USE

Stop us and ask doctor if • condition worsens • symptoms last
more than 7 days or clear up and occurs again within a few days.

Keep out of reach of children. If product is swallowed, get medical help or contact a Poison Control Center right away.

Directions

• Apply as needed. • After cleansing your face, apply a proper amount on skin and spread lightly for absorption.

Inactive Ingredients

Water, Glycerin, Dipropylene Glycol, Cetearyl Alcohol, Butylene Glycol Dicaprylate/Dicaprate, Cyclopentasiloxane, Cetyl Ethylhexanoate, Silica, Cyclohexasiloxane, Butylene Glycol, 1,2-Hexanediol, Dimethicone/Vinyl Dimethicone Crosspolymer, Betaine, Butyrospermum Parkii (Shea) Butter, Glyceryl Stearate, Caprylyl Glycol, Cetearyl Glucoside, Chlorphenesin, PEG-5 Glyceryl Isostearate, Polysorbate 60, PEG-8 Glyceryl Isostearate, Arginine, Carbomer, Citrus Unshiu Peel Extract, Bisabolol, Tocopheryl Acetate, Rosa Centifolia Flower Water, Olivoyl Hydrolyzed Wheat Protein, PEG-20 Glyceryl Isostearate, Polyacrylamide, Glyceryl Oleate, Ethylhexylglycerin, C13-14 Isoparaffin, PEG-40 Hydrogenated Castor Oil, Disodium EDTA, Carrageenan, Laureth-7, Dipotassium Glycyrrhizate, Xanthan Gum, Agar, Potassium Hydroxide, Glucose, Acrylates/C10-30 Alkyl Acrylate Crosspolymer, Iris Ensata Extract, Cosmos Sulphureus Flower/Leaf/Stem Extract, Lilium Candidum Flower Extract, Rosa Centifolia Flower Extract, Jasminum Officinale (Jasmine) Flower Extract, Hibiscus Rosa-Sinensis Flower/Leaf Extract, Sodium Benzoate, Nelumbo Nucifera Flower Extract, Phenoxyethanol, Potassium Sorbate, Sodium Hydroxide, Fragrance, Mica, Titanium Dioxide (CI 77891), Iron Oxide (CI 77491)

Other Information

Protect this product from excessive heat and direct sun.

Questions or Comments?

Call toll free 1-800-311-6680